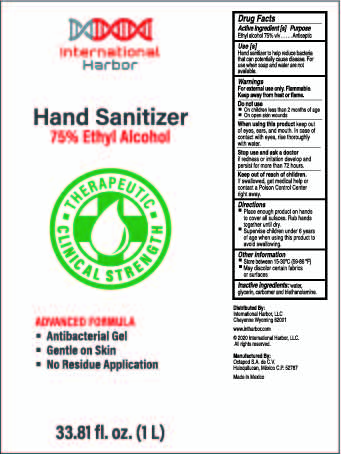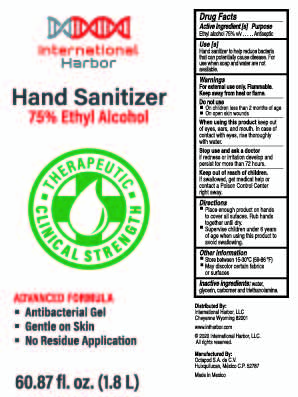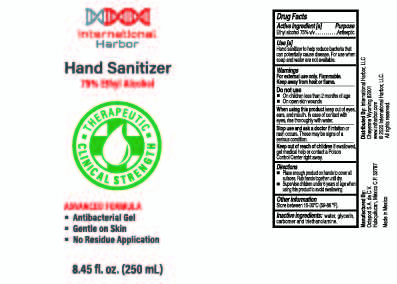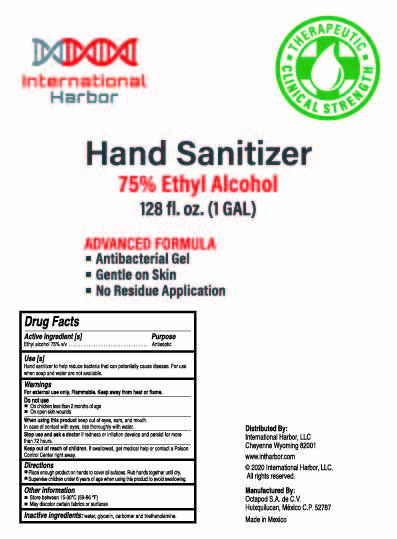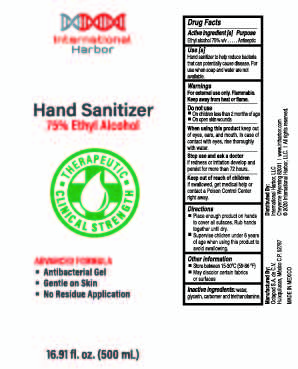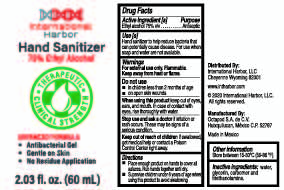 DRUG LABEL: International Harbor
NDC: 79838-003 | Form: GEL
Manufacturer: INTERNATIONAL HARBOR LLC
Category: otc | Type: HUMAN OTC DRUG LABEL
Date: 20200921

ACTIVE INGREDIENTS: ALCOHOL 75 mL/100 mL
INACTIVE INGREDIENTS: GLYCERIN 1 mL/100 mL; CARBOMER 1342 0.45 mL/100 mL; WATER 23.425 mL/100 mL; TRIETHANOLAMINE HYDRIODIDE 0.125 mL/100 mL

International Harbor gel Antibacterial (60 ml, 250 ml, 500 ml, 1 l, 1.8 l 1 gal)

Active Ingredient(s)

Alcohol 75% v/v. Purpose: Antiseptic

Purpose

Antiseptic, Hand Sanitizer

Use

Hand Sanitizer to help reduce bacteria that potentially can cause disease. For use when soap and water are not available.

Warnings

For external use only. Flammable. Keep away from heat or flame

Do not use

- in children less than 2 months of age
- on open skin wounds

When using this product keep out of eyes, ears, and mouth. In case of contact with eyes, rinse eyes thoroughly with water.
Stop use and ask a doctor if irritation or rash occurs. These may be signs of a serious condition.
Keep out of reach of children. If swallowed, get medical help or contact a Poison Control Center right away.

Stop use and ask a doctor if irritation or rash occurs. These may be signs of a serious condition.

Keep out of reach of children. If swallowed, get medical help or contact a Poison Control Center right away.

Directions

- Place enough product on hands to cover all surfaces. Rub hands together until dry.
- Supervise children under 6 years of age when using this product to avoid swallowing.

Other information

- Store between 15-30C (59-86F)
- Avoid freezing and excessive heat above 40C (104F)

Inactive ingredients

water, glycerin, carbomer, triethanolamine.

PACKAGE LABEL

PDP 60 ml NDC:79838-003-01

PDP 250 ml NDC:79838-003-02

PDP 500 ml NDC:79838-003-03

PDP 1000 ml NDC:79838-003-04

PDP 1800 ml NDC:79838-003-05

PDP 3785 ml NDC:79838-003-06